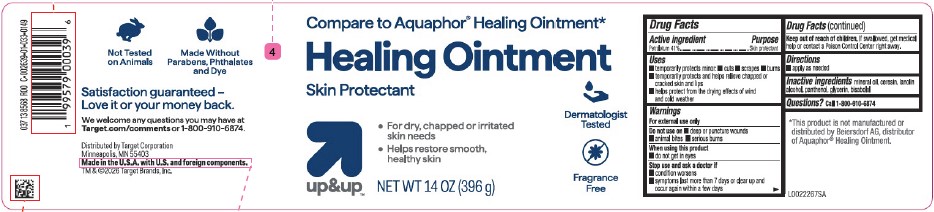 DRUG LABEL: Advanced Healing
NDC: 82442-247 | Form: OINTMENT
Manufacturer: Target Corporation
Category: otc | Type: HUMAN OTC DRUG LABEL
Date: 20260218

ACTIVE INGREDIENTS: PETROLATUM 410 mg/1 g
INACTIVE INGREDIENTS: PANTHENOL; GLYCERIN; LANOLIN ALCOHOLS; MINERAL OIL; CERESIN; LEVOMENOL

Up & Up 247.000/247AA-AC
Healing Ointment for Dry and Cracked Skin

Active ingredient

Petrolatum 41%

Purpose

Skin protectant

Uses

- temporarily protects minor: •cuts •scrapes burns
- temporarily protects and helps relieve chapped or cracked skin and lips
- helps protect from the drying effects of wind and cold weather

Warnings

For external use only

Do not use on

- deep or puncture wounds
- animal bites
- serious burns

When using this product

- do not get in eyes

Stop use and ask a doctor if

- condition worsens
- symptoms last more than 7 days or clear up and occur again within a few days

Keep out of reach of children.

If swallowed, get medical help or contract a Poison Control Center right away.

Directions

- apply as needed

Inactive ingredients

mineral oil, ceresin, lanolin alcohol, panthenol, glycerin, bisabolol

Questions?

Call 1-800-910-6874

Disclaimer

*This product is not manufactured or distributed by Beiersdorf Inc., distributor of Aquaphor®Healing Ointment.

Claims

Not Tested on Animals

Made Without Parabens, Phthalates and Dye

Adverse Reaction

Satisfaction guaranteed - Love it or your money back.

We welcome any questions you may have at Target.com/comments or 1-800-910-6874.

Distributed by Target Corporation

Minneapolis, MN 55403

Made in the U.S.A. with U.S. and foreign components.

TM & ©2026 Target Brands, Inc.

Principal Display Panel

Compare to Aquaphor®Healing Ointment*

Healing Ointment

Skin Protectant

- For dry, chapped or irritated skin needs
- Helps restore smooth, healthy skin

Dermatologist Tested

Fragrance Free

up & up™

NET WT 14 OZ (396 g)